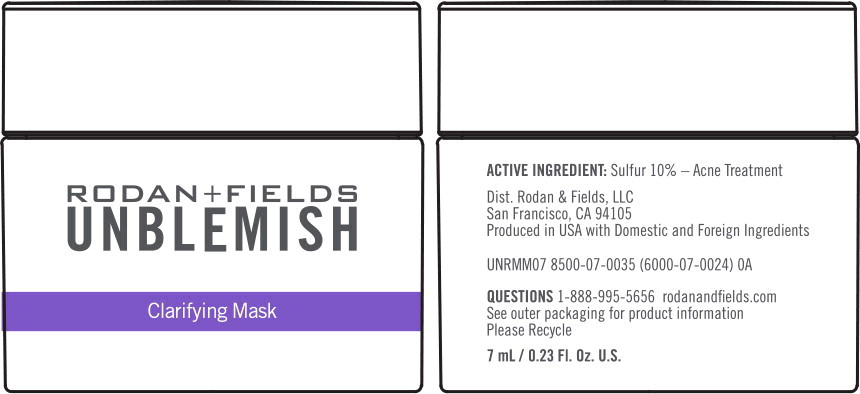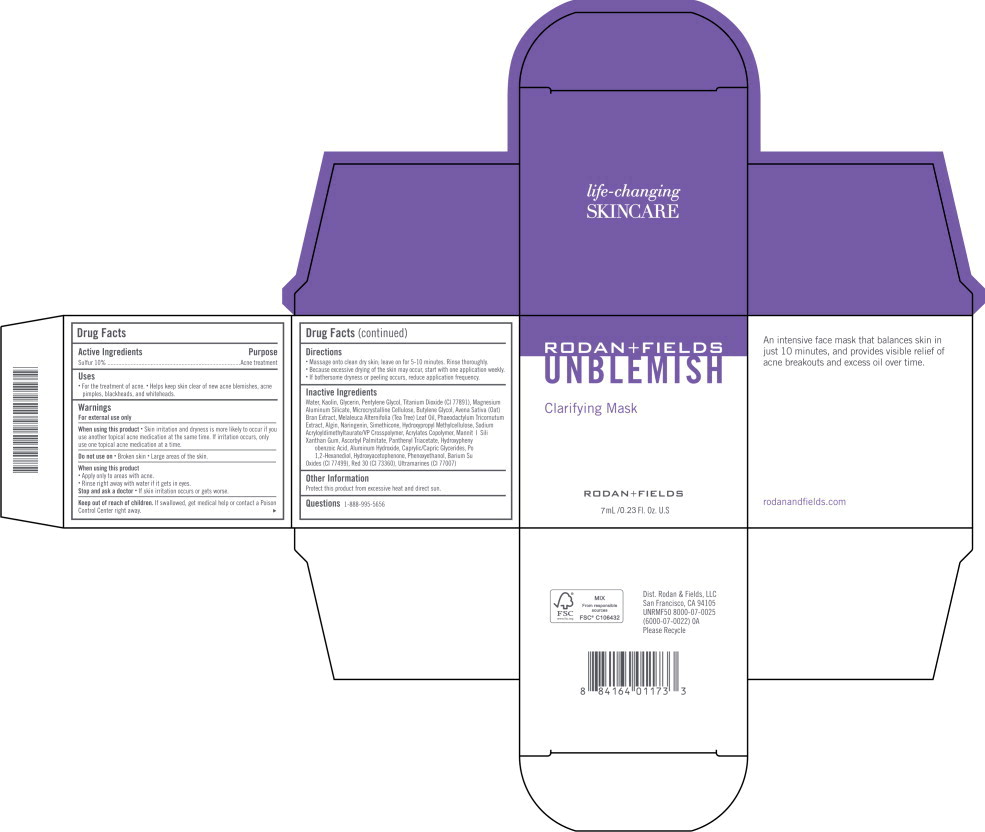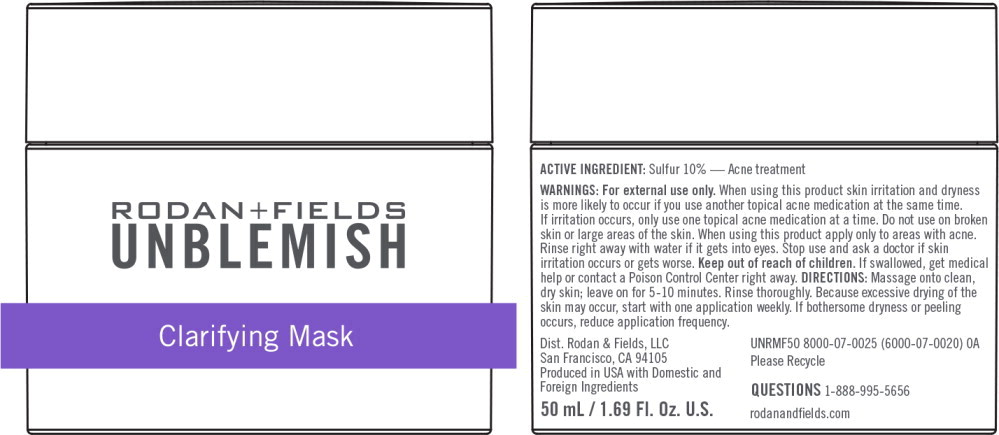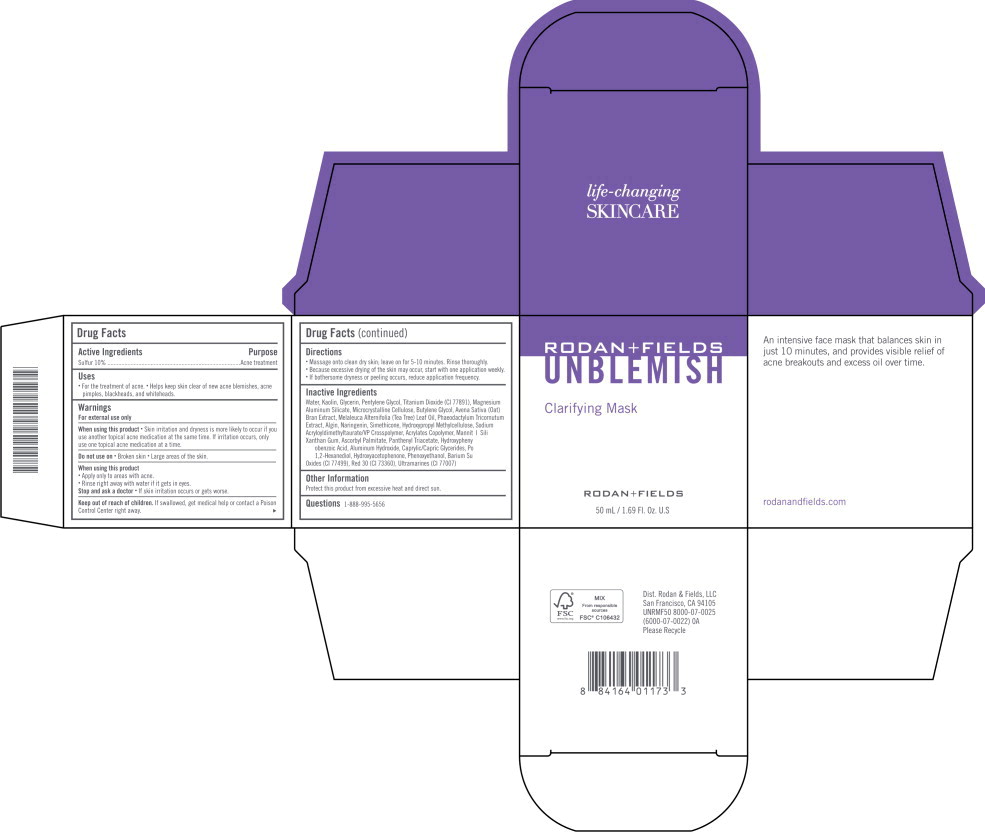 DRUG LABEL: UNBLEMISH Clarifying Mask
NDC: 14222-2140 | Form: CREAM
Manufacturer: Rodan & Fields
Category: otc | Type: HUMAN OTC DRUG LABEL
Date: 20251215

ACTIVE INGREDIENTS: SULFUR 0.1 g/1 mL
INACTIVE INGREDIENTS: WATER; KAOLIN; GLYCERIN; PENTYLENE GLYCOL; TITANIUM DIOXIDE; MAGNESIUM ALUMINUM SILICATE; MICROCRYSTALLINE CELLULOSE; BUTYLENE GLYCOL; NARINGENIN; TEA TREE OIL; OAT BRAN; HYDROXYPHENYL PROPAMIDOBENZOIC ACID; MANNITOL; PANTHENOL TRIACETATE, (+)-; HYPROMELLOSE, UNSPECIFIED; XANTHAN GUM; MEDIUM-CHAIN TRIGLYCERIDES; POLYSORBATE 20; SODIUM ALGINATE; 1,2-HEXANEDIOL; ASCORBYL PALMITATE; HYDROXYACETOPHENONE; CAPRYLYL GLYCOL; PHENOXYETHANOL; ALUMINUM HYDROXIDE; BARIUM SULFATE; SILICON DIOXIDE; FERROSOFERRIC OXIDE; D&C RED NO. 30; ULTRAMARINE BLUE; LIMONENE, (+)-; LINALOOL, (+/-)-; .BETA.-CITRONELLOL, (R)-; GERANIOL

Drug Facts

Active Ingredients

Sulfur 10%

Purpose

Acne treatment

Uses

- For the treatment of acne.
- Helps keep skin clear of new acne blemishes, acne pimples, blackheads, and whiteheads.

Warnings

For external use only

When using this product

- Skin irritation and dryness is more likely to occur if you use another topical acne medication at the same time. If irritation occurs, only use on topical acne medication at a time.

Do not use on

- Broken skin
- Large areas of the skin.

When using this product

- Apply only to areas with acne.
- Rinse right away with if it gets in eyes.

Stop and ask a doctor

- if skin irritation occurs or get worse.

Keep out of reach of children.

If swallowed, get medical help or contact a Poison Control Center right away.

Directions

- Massage onto clean dry skin; leave on for 5-10 minutes. Rinse thoroughly.
- Because excessive drying of the skin may occur, start with one application weekly.
- If bothersome dryness or peeling occurs, reduce application frequency.

Inactive Ingredients

Water, Kaolin, Glycerin, Pentylene Glycol, Titanium Dioxide (CI 77891), Magnesium Aluminum Silicate, Microcrystalline Cellulose, Butylene Glycol, Naringenin, Phaeodactylum Tricornutum Extract, Melaleuca Alternifolia (Tea Tree) Leaf Oil, Avena Sativa (Oat) Bran Extract, Hydroxyphenyl Propamidobenzoic Acid, Simethicone, Mannitol, Panthenyl Triacetate, Sodium Acryloyldimethyltaurate/VP Crosspolymer, Acrylates Copolymer, Hydroxypropyl Methylcellulose, Xanthan Gum, Caprylic/Capric Glycerides, Polysorbate 20, Algin, 1,2-Hexanediol, Ascorbyl Palmitate, Hydroxyacetophenone, Caprylyl Glycol, Phenoxyethanol, Aluminum Hydroxide, Barium Sulfate, Silica, Iron Oxides (CI 77499), Red 30 (CI 73360), Ultramarines (CI 77007).

Other Information

Protect this product from excessive heat and direct sun.

Questions

1-888-995-5656

Principal Display Panel - Unblemish Clarifying Mask 7 mL Jar Label

RODAN+FIELDS

UNBLEMISH

Clarifying Mask

Principal Display Panel - Unblemish Clarifying Mask 7 mL Carton Label

RODAN+FIELDS

UNBLEMISH

Clarifying Mask

RODAN+FIELDS

7 mL/0.23 FL Oz. U.S

Principal Display Panel - Unblemish Clarifying Mask 50 mL Jar Label

RODAN+FIELDS

UNBLEMISH

Clarifying Mask

Principal Display Panel - Unblemish Clarifying Mask 50 mL Carton Label

RODAN+FIELDS

UNBLEMISH

Clarifying Mask

RODAN+FIELDS

50 mL/1.69 FL Oz. U.S